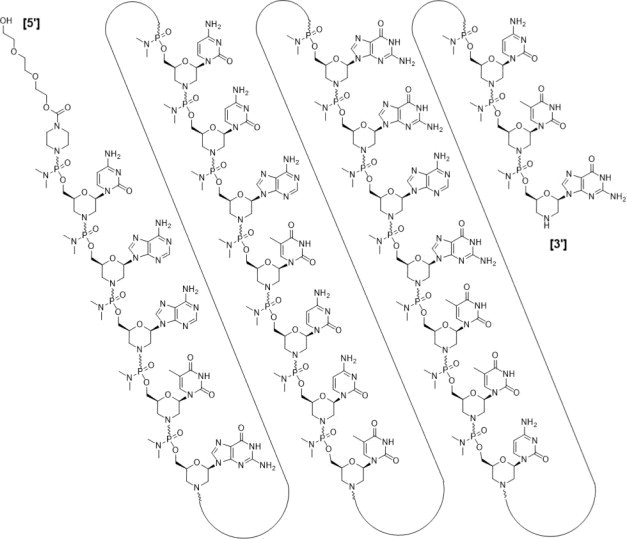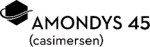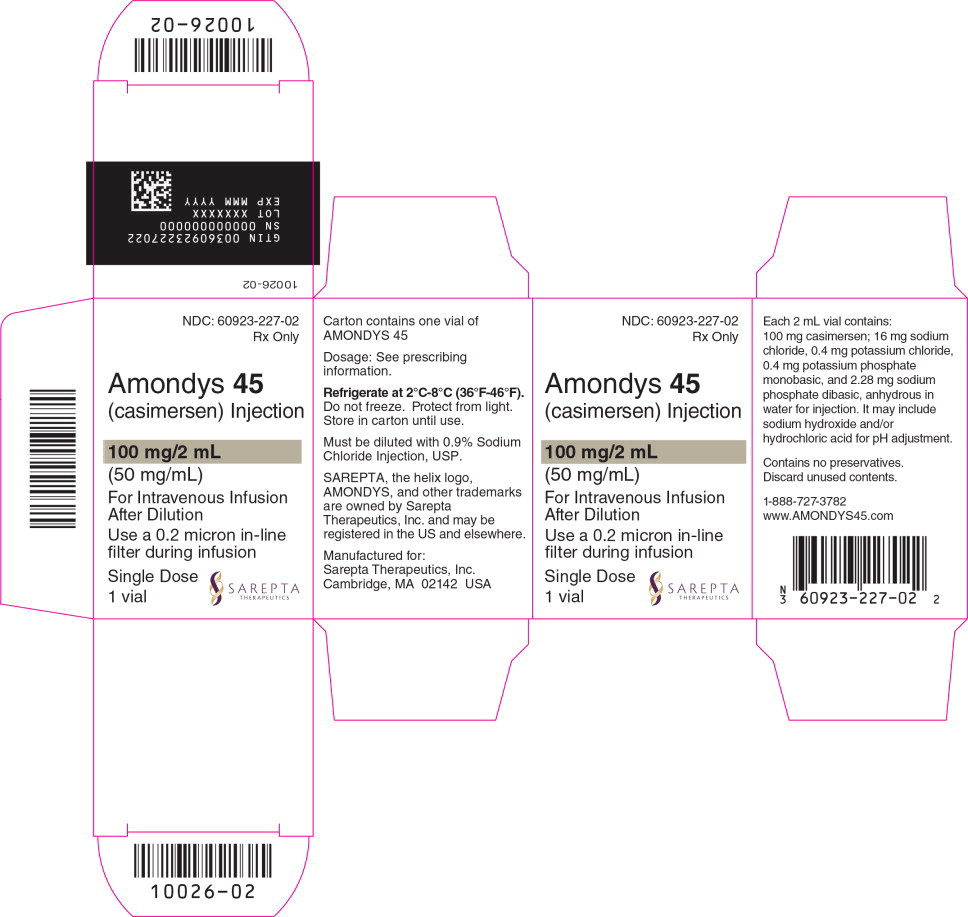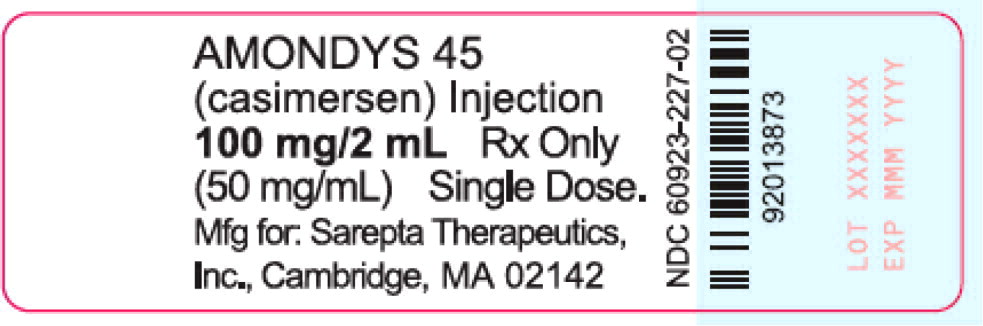 DRUG LABEL: AMONDYS 45
NDC: 60923-227 | Form: INJECTION
Manufacturer: Sarepta Therapeutics, Inc.
Category: prescription | Type: HUMAN PRESCRIPTION DRUG LABEL
Date: 20260109

ACTIVE INGREDIENTS: casimersen 50 mg/1 mL
INACTIVE INGREDIENTS: sodium chloride; potassium chloride; potassium phosphate, monobasic; sodium phosphate, dibasic, anhydrous; sodium hydroxide; hydrochloric acid; water

HIGHLIGHTS OF PRESCRIBING INFORMATION

These highlights do not include all the information needed to use AMONDYS 45® safely and effectively. See full prescribing information for AMONDYS 45.
AMONDYS 45 (casimersen) injection, for intravenous use
Initial U.S. Approval: 2021

1 INDICATIONS AND USAGE

AMONDYS 45 is an antisense oligonucleotide indicated for the treatment of Duchenne muscular dystrophy (DMD) in patients who have a confirmed mutation of the DMD gene that is amenable to exon 45 skipping. This indication is approved under accelerated approval based on an increase in dystrophin production in skeletal muscle observed in patients treated with AMONDYS 45 [see Clinical Studies (14)]. Continued approval for this indication may be contingent upon verification of a clinical benefit in confirmatory trials. (1)

2 DOSAGE AND ADMINISTRATION

- Serum cystatin C, urine dipstick, and urine protein-to-creatinine ratio should be measured before starting AMONDYS 45 (2.1)
- 30 milligrams per kilogram of body weight once weekly (2.2)
- Administer as an intravenous (IV) infusion over 35 to 60 minutes via an in-line 0.2 micron filter (2.2, 2.4)
- Dilution required prior to administration (2.3)

3 DOSAGE FORMS AND STRENGTHS

Injection: 100 mg/2 mL in a single-dose vial (3)

4 CONTRAINDICATIONS

AMONDYS 45 is contraindicated in patients with serious hypersensitivity to casimersen or to any of the inactive ingredients in AMONDYS 45. (4, 5.1)

5 WARNINGS AND PRECAUTIONS

- Hypersensitivity Reactions: Hypersensitivity reactions, including angioedema and anaphylaxis, have occurred in patients who were treated with AMONDYS 45. If a hypersensitivity reaction occurs, institute appropriate medical treatment and consider slowing the infusion, interrupting or discontinuing the AMONDYS 45 infusion (2.4, 5.1)
- Kidney Toxicity: Based on animal data, may cause kidney toxicity. Kidney function should be monitored; creatinine may not be a reliable measure of renal function in DMD patients. (5.2, 13.2)

6 ADVERSE REACTIONS

The most common adverse reactions (incidence >20% and at least 5% higher than placebo) were upper respiratory tract infection, cough, pyrexia, headache, arthralgia, and oropharyngeal pain. (6.1)

To report SUSPECTED ADVERSE REACTIONS, contact Sarepta Therapeutics, Inc. at 1-888-SAREPTA (1-888-727-3782) or FDA at 1-800-FDA-1088 or www.fda.gov/medwatch.

FULL PRESCRIBING INFORMATION

1 INDICATIONS AND USAGE

AMONDYS 45 is indicated for the treatment of Duchenne muscular dystrophy (DMD) in patients who have a confirmed mutation of the DMD gene that is amenable to exon 45 skipping. This indication is approved under accelerated approval based on an increase in dystrophin production in skeletal muscle observed in patients treated with AMONDYS 45 [see Clinical Studies (14)]. Continued approval for this indication may be contingent upon verification of a clinical benefit in confirmatory trials.

2 DOSAGE AND ADMINISTRATION

2.1 Monitoring to Assess Safety

Serum cystatin C, urine dipstick, and urine protein-to-creatinine ratio (UPCR) should be measured before starting AMONDYS 45. Consider measurement of glomerular filtration rate prior to initiation of AMONDYS 45. Monitoring for kidney toxicity during treatment is recommended. Obtain the urine sample prior to infusion of AMONDYS 45 or at least 48 hours after infusion [see Warnings and Precautions (5.2)].

2.2 Dosing Information

The recommended dosage of AMONDYS 45 is 30 milligrams per kilogram administered once weekly as a 35 to 60-minute intravenous infusion via an in-line 0.2 micron filter.

If a dose of AMONDYS 45 is missed, it may be administered as soon as possible after the scheduled dose.

2.3 Preparation Instructions

AMONDYS 45 is supplied in single-dose vials as a preservative-free concentrated solution that requires dilution prior to administration. Parenteral drug products should be inspected visually for particulate matter and discoloration prior to administration, whenever solution and container permit. Use aseptic technique.

1. Calculate the total dose of AMONDYS 45 to be administered based on the patient's weight and the recommended dose of 30 milligrams per kilogram. Determine the volume of AMONDYS 45 needed and the correct number of vials to supply the full calculated dose.
2. Allow the vials to warm to room temperature. Mix the contents of each vial by gently inverting 2 or 3 times. Do not shake.
3. Visually inspect each vial of AMONDYS 45. The solution is a clear to slightly opalescent, colorless liquid, and may contain trace amounts of small, white to off-white amorphous particles. Do not use if the solution in the vials is cloudy, discolored or contains extraneous particulate matter other than trace amounts of small, white to off-white amorphous particles.
4. With a syringe fitted with a 21-gauge or smaller bore non-coring needle, withdraw the calculated volume of AMONDYS 45 from the appropriate number of vials. To avoid dulling the needle and fragmenting the stoppers, replace the needle periodically during preparation.
5. Dilute the withdrawn AMONDYS 45 in 0.9% Sodium Chloride Injection, USP, to make a total volume of 100 to 150 mL. Gently invert 2 to 3 times to mix. Do not shake. Visually inspect the diluted solution. Do not use if the solution is cloudy, discolored or contains extraneous particulate matter other than trace amounts of small, white to off-white amorphous particles.
6. Administer the diluted solution via an in-line 0.2 micron filter.
7. AMONDYS 45 contains no preservatives and should be administered immediately after dilution. Complete infusion of diluted AMONDYS 45 within 4 hours of dilution. If immediate use is not possible the diluted product may be stored for up to 24 hours at 2 °C to 8 °C (36 °F to 46 °F). Do not freeze. Discard unused AMONDYS 45.

2.4 Administration Instructions

Application of a topical anesthetic cream to the infusion site prior to administration of AMONDYS 45 may be considered.

AMONDYS 45 is administered via intravenous infusion. Flush the intravenous access line with 0.9% Sodium Chloride Injection, USP, prior to and after infusion.

Infuse the diluted AMONDYS 45 over 35 to 60 minutes via an in-line 0.2 micron filter. Do not mix other medication with AMONDYS 45 or infuse other medications concomitantly via the same intravenous access with AMONDYS 45.

If a hypersensitivity reaction occurs, consider slowing the infusion, interrupting or discontinuing the AMONDYS 45 therapy [see Contraindications (4), Warning and Precautions (5.1) and Adverse Reactions (6.2)].

3 DOSAGE FORMS AND STRENGTHS

AMONDYS 45 is a clear to slightly opalescent, colorless liquid and may contain trace amounts of small, white to off-white amorphous particles and is available as:

- Injection: 100 mg/2 mL (50 mg/ mL) solution in a single-dose vial

4 CONTRAINDICATIONS

AMONDYS 45 is contraindicated in patients with known serious hypersensitivity to casimersen or to any of the inactive ingredients in AMONDYS 45. Instances of hypersensitivity, including angioedema and anaphylaxis, have occurred in patients receiving AMONDYS 45 [see Warnings and Precautions (5.1)].

5 WARNINGS AND PRECAUTIONS

5.1 Hypersensitivity Reactions

Hypersensitivity reactions, including angioedema and anaphylaxis, have occurred in patients who were treated with AMONDYS 45. If a hypersensitivity reaction occurs, institute appropriate medical treatment, and consider slowing the infusion [see Dosage and Administration (2.4)], interrupting, or discontinuing the AMONDYS 45 infusion and monitor until the condition resolves. AMONDYS 45 is contraindicated in patients with known serious hypersensitivity to casimersen or to any of the inactive ingredients in AMONDYS 45 [see Contraindications (4)].

5.2 Kidney Toxicity

Kidney toxicity was observed in animals who received casimersen [see Use in Specific Populations (8.4) and Nonclinical Toxicology (13.2)]. Although kidney toxicity was not observed in the clinical studies with AMONDYS 45, kidney toxicity, including potentially fatal glomerulonephritis, has been observed after administration of some antisense oligonucleotides. Kidney function should be monitored in patients taking AMONDYS 45. Because of the effect of reduced skeletal muscle mass on creatinine measurements, creatinine may not be a reliable measure of kidney function in DMD patients. Serum cystatin C, urine dipstick, and urine protein-to-creatinine ratio should be measured before starting AMONDYS 45. Consider also measuring glomerular filtration rate using an exogenous filtration marker before starting AMONDYS 45. During treatment, monitor urine dipstick every month, and serum cystatin C and urine protein-to-creatinine ratio (UPCR) every three months. Only urine expected to be free of excreted AMONDYS 45 should be used for monitoring of urine protein. Urine obtained on the day of AMONDYS 45 infusion prior to the infusion, or urine obtained at least 48 hours after the most recent infusion, may be used. Alternatively, use a laboratory test that does not use the reagent pyrogallol red, as this reagent has the potential to cross react with any AMONDYS 45 that is excreted in the urine and thus lead to a false positive result for urine protein.

If a persistent increase in serum cystatin C or proteinuria is detected, refer to a pediatric nephrologist for further evaluation.

6 ADVERSE REACTIONS

The following clinically significant adverse reactions are described elsewhere in the labeling:

- Hypersensitivity reactions [see Warnings and Precautions (5.1)]

6.1 Clinical Trials Experience

Because clinical trials are conducted under widely varying conditions, adverse reaction rates observed in clinical trials of a drug cannot be directly compared to rates in the clinical trials of another drug and may not reflect the rates observed in practice.

In the AMONDYS 45 clinical development program, 76 patients received at least one intravenous dose of AMONDYS 45 (30 mg/kg). All patients were male and had genetically confirmed Duchenne muscular dystrophy. Age at study entry was 7 to 20 years (mean 9.9 years). Most (88%) patients were White, and 9% were Asian.

AMONDYS 45 was studied in a double-blind, placebo-controlled study (Study 1).

Patients in ongoing Study 1 received AMONDYS 45 (n=57) 30 mg/kg or placebo (n=31) intravenously once weekly for up to 96 weeks, after which all patients received or will receive AMONDYS 45 30 mg/kg for up to 48 weeks.

Adverse reactions observed in ≥20% of patients treated with AMONDYS 45 and 5% more frequently than in the placebo group in Study 1 are shown in Table 1.

Table 1. Adverse Reactions Occurring in at Least 20% of Patients Treated with AMONDYS 45 and at a Rate at Least 5% More Frequently than in the Placebo Group in Study 1
Adverse Reaction | AMONDYS 45 30 mg/kg Once Weekly (n = 57) % | Placebo (n = 31) %
Upper Respiratory Tract Infections* | 65 | 55
Cough | 33 | 26
Pyrexia | 33 | 23
Headache | 32 | 19
Arthralgia | 21 | 10
Oropharyngeal Pain | 21 | 7
*Includes upper respiratory infection, pharyngitis, nasopharyngitis, and rhinitis.

Other adverse reactions that occurred in at least 10% of patients treated with AMONDYS 45, and that were reported at a rate at least 5% more frequently in the AMONDYS 45 group than in the placebo group, were: ear pain, nausea, ear infection, post-traumatic pain, and dizziness and light-headedness.

6.2 Postmarketing Experience

The following adverse reactions have been identified during postapproval use of AMONDYS 45. Because these reactions are reported voluntarily from a population of uncertain size, it is not always possible to reliably estimate their frequency or establish a causal relationship to drug exposure. Infusion-related reactions including rash, headache, cough, abdominal pain (including upper abdominal pain), and vomiting occurred within 24 hours from the start of an infusion of AMONDYS 45.

Hypersensitivity reactions, including angioedema and anaphylaxis, have occurred in patients treated with AMONDYS 45.

8 USE IN SPECIFIC POPULATIONS

8.1 Pregnancy

Risk Summary

There are no human or animal data available to assess the use of AMONDYS 45 during pregnancy. In the U.S. general population, major birth defects occur in 2% to 4% and miscarriage occurs in 15% to 20% of clinically recognized pregnancies.

8.2 Lactation

Risk Summary

There are no human or animal data to assess the effect of AMONDYS 45 on milk production, the presence of casimersen in milk, or the effects of AMONDYS 45 on the breastfed infant.

The developmental and health benefits of breastfeeding should be considered along with the mother's clinical need for AMONDYS 45 and any potential adverse effects on the breastfed infant from AMONDYS 45 or from the underlying maternal condition.

8.4 Pediatric Use

AMONDYS 45 is indicated for the treatment of DMD in patients who have a confirmed mutation of the DMD gene that is amenable to exon 45 skipping, including pediatric patients [see Clinical Studies (14)].

Juvenile Animal Toxicity Data

Intravenous administration of casimersen (0, 100, 300, and 900 mg/kg) to juvenile male rats once weekly for 10 weeks (postnatal days 14 to 77) resulted in renal tubular degeneration/necrosis at the highest dose tested. No effects were observed on the male reproductive system, neurobehavioral development, or immune function. At the overall no-effect dose (300 mg/kg), plasma exposure (AUC) was 4 times that in humans at the recommended human dose of 30 mg/kg/week.

8.5 Geriatric Use

DMD is largely a disease of children and young adults; therefore, there is no experience with AMONDYS 45 in geriatric DMD patients.

8.6 Patients with Renal Impairment

Renal clearance of casimersen is decreased in non-DMD adults with renal impairment based on estimated glomerular filtration rate (calculated using the Modification of Diet and Renal Disease (MDRD) equation) [see Clinical Pharmacology (12.3)]. However, because of the effect of reduced skeletal muscle mass on creatinine measurements in DMD patients, no specific dosage adjustment can be recommended for DMD patients with renal impairment based on estimated glomerular filtration rate. Patients with known renal function impairment should be closely monitored during treatment with AMONDYS 45.

11 DESCRIPTION

AMONDYS 45 (casimersen) injection is a sterile, aqueous, preservative-free, concentrated solution for dilution prior to intravenous administration. AMONDYS 45 is a clear to slightly opalescent, colorless liquid and may contain trace amounts of small, white to off-white amorphous particles. AMONDYS 45 is supplied in single-dose vials containing 100 mg casimersen (50 mg/mL). AMONDYS 45 is formulated as an isotonic phosphate buffered saline solution with an osmolality of 260 to 320 mOsm and a pH of 7.5. Each milliliter of AMONDYS 45 contains: 50 mg casimersen; 0.2 mg potassium chloride; 0.2 mg potassium phosphate monobasic; 8 mg sodium chloride; and 1.14 mg sodium phosphate dibasic, anhydrous, in water for injection. The product may contain hydrochloric acid or sodium hydroxide to adjust pH.

Casimersen is an antisense oligonucleotide of the phosphorodiamidate morpholino oligomer (PMO) subclass. PMOs are synthetic molecules in which the five-membered ribofuranosyl rings found in natural DNA and RNA are replaced by a six-membered morpholino ring. Each morpholino ring is linked through an uncharged phosphorodiamidate moiety rather than the negatively charged phosphate linkage that is present in natural DNA and RNA. Each phosphorodiamidate morpholino subunit contains one of the heterocyclic bases found in DNA (adenine, cytosine, guanine, or thymine). Casimersen contains 22 linked subunits. The sequence of bases from the 5' end to 3' end is CAATGCCATCCTGGAGTTCCTG. The molecular formula of casimersen is C268H424N124O95P22 and the molecular weight is 7584.5 daltons.

The structure of casimersen is:

12 CLINICAL PHARMACOLOGY

12.1 Mechanism of Action

Casimersen is designed to bind to exon 45 of dystrophin pre-mRNA resulting in exclusion of this exon during mRNA processing in patients with genetic mutations that are amenable to exon 45 skipping. Exon 45 skipping is intended to allow for production of an internally truncated dystrophin protein in patients with genetic mutations that are amenable to exon 45 skipping [see Clinical Studies (14)].

12.2 Pharmacodynamics

In the interim analysis of muscle biopsy tissue obtained at baseline and at Week 48 from patients in Study 1, patients who received AMONDYS 45 (n=27) demonstrated a significant increase in skipping of exon 45 (p<0.001) compared to baseline, demonstrated by reverse transcription digital droplet polymerase chain reaction (RT-ddPCR). Patients who received placebo (n=16) did not demonstrate a significant increase in exon 45 skipping (p=0.808). The level of exon skipping is positively correlated with dystrophin protein expression [see Clinical Studies (14)].

In Study 1 [see Clinical Studies (14)], dystrophin levels as assessed by the Sarepta Western blot assay increased from 0.93% (SD 1.67) of normal at baseline to 1.74% (SD 1.97) of normal after 48 weeks of treatment with AMONDYS 45. The mean change from baseline in dystrophin after 48 weeks of treatment with AMONDYS 45 was 0.81% (SD 0.70) of normal levels (p<0.001). This increase in dystrophin protein expression after treatment with AMONDYS 45 positively correlated with the level of exon skipping. The mean change from baseline in dystrophin after 48 weeks of treatment with placebo was 0.22% (SD 0.49). Patients who received AMONDYS 45 showed a significantly greater increase in dystrophin protein levels from baseline to Week 48 compared to those who received placebo (mean difference of 0.59%; p = 0.004). Dystrophin levels assessed by Western blot can be meaningfully influenced by differences in sample processing, analytical technique, reference materials, and quantitation methodologies. Therefore, comparing dystrophin results from different assay protocols will require a standardized reference material and additional bridging studies.

Correct localization of dystrophin to the sarcolemma in patients treated with AMONDYS 45 was demonstrated by immunofluorescence staining.

12.3 Pharmacokinetics

The pharmacokinetics of casimersen was evaluated in DMD patients following administration of intravenous (IV) doses ranging from 4 mg/kg/week to 30 mg/kg/week (i.e., recommended dosage). Following a single IV dose of casimersen, Cmax was reached at the end of infusion. Casimersen exposure increased in a proportional manner with dose increment. No accumulation of casimersen was observed in plasma following once weekly dosing. Inter-subject variability (as %CV) for casimersen Cmax and AUC ranged from 12% to 34% and 16% to 34%, respectively.

Distribution

Binding of casimersen to human plasma protein was not concentration-dependent and ranged from 8.4% to 31.6%. The mean apparent volume of distribution at steady state (Vss) was 367 mL/kg (%CV = 28.9) following a 30 mg/kg dose of casimersen administered intravenously.

Elimination

The plasma clearance (CL) of casimersen was 180 mL/hr/kg at the 30 mg/kg dose. The elimination half-life (t1/2) was 3.5 hours (SD 0.4 hours).

Metabolism

Casimersen is metabolically stable in human hepatic microsomal incubations. No metabolites were detected in plasma or urine.

Excretion

Casimersen is mostly excreted unchanged in the urine. In a clinical study with radiolabeled casimersen, more than 90% of the drug was excreted in urine, with negligible fecal excretion.

Specific Populations

Age, Sex & Race

The pharmacokinetics of AMONDYS 45 have been evaluated in male DMD patients 9 to 20 years of age. There is no experience with the use of AMONDYS 45 in DMD patients 65 years of age or older. AMONDYS 45 has not been studied in female patients. The potential impact of race on the pharmacokinetics of casimersen is unknown.

Patients with Renal Impairment

The effect of renal impairment on the pharmacokinetics of casimersen was evaluated in non-DMD subjects aged 35 to 65 years with Stage 2 chronic kidney disease (CKD) (n=8, estimated glomerular filtration rate [eGFR] ≥60 and <90 mL/min/1.73 m^2) or Stage 3 CKD (n=8, eGFR ≥30 and <60 mL/min/1.73 m^2) and matched healthy subjects (n=9, eGFR ≥90 mL/min/1.73 m^2). Subjects received a single 30 mg/kg intravenous dose of casimersen.

In subjects with Stage 2 or Stage 3 CKD, exposure (AUC) increased approximately 1.2-fold and 1.8-fold, respectively, compared with subjects with normal renal function. The Cmax in subjects with Stage 2 CKD was similar to Cmax in subjects with normal renal function; in subjects with Stage 3 CKD, there was a 1.2-fold increase in Cmax compared with subjects with normal renal function. The effect of Stage 4 or Stage 5 CKD on casimersen pharmacokinetics and safety has not been studied.

Estimated GFR values derived from MDRD equations and the threshold definitions for various CKD stages in otherwise healthy adults would not be generalizable to pediatric patients with DMD. Therefore, no specific dosage adjustment can be recommended for patients with renal impairment [see Use in Specific Populations (8.6)].

Patients with Hepatic Impairment

AMONDYS 45 has not been studied in patients with hepatic impairment. However, casimersen does not undergo hepatic metabolism, and the systemic clearance of casimersen is not expected to be affected by hepatic impairment.

Drug Interaction Studies

Based on in vitro data, casimersen has a low potential for clinically relevant drug-drug interactions with major CYP enzymes and transporters.

Casimersen did not inhibit CYP1A2, CYP2B6, CYP2C8, or CYP2D6 in vitro. Casimersen was a potential inhibitor of CYP3A4/5, CYP2C9, and CYP2C19 in vitro; however, considering its short plasma half-life and lack of plasma accumulation with the weekly dosing regimen, clinical drug interaction with substrates for these enzymes is unlikely. Casimersen did not induce CYP1A2, CYP2B6, or CYP3A4 either at the mRNA or protein (activity) level. Casimersen was not metabolized by human hepatic microsomes and was not a substrate or strong inhibitor of the key human drug transporters tested (OAT1, OAT3, OCT2, OATP1B1, OATP1B3, MATE1, MATE2-K, P-gp, BCRP, and MRP2).

13 NONCLINICAL TOXICOLOGY

13.1 Carcinogenesis, Mutagenesis, Impairment of Fertility

Carcinogenesis

Administration of casimersen to male transgenic (Tg.rasH2) mice (0, 100, 300, or 1000 mg/kg) weekly for 26 weeks by subcutaneous injection and to male rats (0, 125, 250, or 500 mg/kg) for up to 104 weeks by intravenous injection resulted in no increase in neoplasms.

Mutagenesis

Casimersen was negative in in vitro (bacterial reverse mutation assay and chromosomal aberration assay in CHO cells) and in vivo (mouse bone marrow micronucleus) assays.

Impairment of Fertility

Fertility studies in animals were not conducted with casimersen. No effects of casimersen were observed on the male reproductive system following weekly administration to male mice at subcutaneous doses up to 960 mg/kg for 26 weeks or to male monkeys at intravenous doses up to 640 mg/kg for 39 weeks. Plasma exposures at the highest doses tested in mouse and monkey were approximately 9 and 35 times, respectively, that in humans at the recommended human dose of 30 mg/kg/week.

13.2 Animal Toxicology and/or Pharmacology

Kidney toxicity was observed in studies in male mice and rats [see Warnings and Precautions (5.1)].

In male mice, casimersen was administered weekly for 12 weeks (0, 12, 120, or 960 mg/kg) or 22 weeks (0, 300, 960, or 2000 mg/kg) by intravenous injection or for 26 weeks by subcutaneous injection (0, 300, 600, or 960 mg/kg). In the 12-week study, microscopic findings in kidney (cytoplasmic basophilia and microvacuolation) were observed at the highest dose tested. In the 22- and 26-week studies, renal tubular degeneration was observed at all doses. A no-effect dose for adverse effects on kidney was not identified. Plasma exposure (AUC) at the lowest dose tested in the 26-week study (300 mg/kg) was approximately 2 times that in humans at the recommended human dose (RHD) of 30 mg/kg/week.

In male rats, intravenous administration of casimersen (0, 250, 500, 1000, or 2000 mg/kg) weekly for 13 weeks resulted in renal tubular degeneration at all doses tested; at the highest dose, the microscopic changes were accompanied by increases in blood urea nitrogen. A no-effect dose for adverse effects on kidney was not identified. Plasma exposure (AUC) at the lowest dose tested were approximately 4 times that in humans at the RHD.

14 CLINICAL STUDIES

The effect of AMONDYS 45 on dystrophin production was evaluated in one study in male DMD patients who have a confirmed mutation of the DMD gene that is amenable to exon 45 skipping (Study 1; NCT02500381).

Study 1 is an ongoing, double-blind, placebo-controlled, multicenter study designed to evaluate the safety and efficacy of AMONDYS 45 in ambulatory patients. The study is planned to enroll a total of 111 patients, age 7 to 13 years, randomized to AMONDYS 45 or placebo in a 2 to 1 ratio. Patients were required to have been on a stable dose of oral corticosteroids for at least 24 weeks prior to dosing with AMONDYS 45 or placebo. Following the 96-week double-blind period, all patients began or are to begin an additional 48 week open-label treatment period. Interim efficacy was assessed based on change from baseline in the dystrophin protein level (measured as % of the dystrophin level in healthy subjects, i.e., % of normal) at Week 48 of Study 1. Interim results from 43 evaluable patients (n = 27, AMONDYS 45; n = 16, placebo) who had a muscle biopsy at Week 48 of the double-blind period are presented in Table 2. Patients who provided muscle biopsy data had a median age of 9 years and were 86% White.

Table 2. Dystrophin Levels (% of Normal) at Baseline and at Week 48 from Muscle Biopsy Interim Results in Study 1
 | Placebo | AMONDYS 45 30 mg/kg/week IV
Dystrophin by Sarepta Western blot | n=16 | n=27
Baseline Mean (SD) | 0.54 (0.79) | 0.93 (1.67)
Week 48 Mean (SD) | 0.76 (1.15) | 1.74 (1.97)
Change from Baseline Mean (SD) | 0.22 (0.49) | 0.81 (0.70)
p-value Change from Baseline to Week 48 | 0.09 | <0.001
Between group mean difference | 0.59
p-value between groups | p=0.004

16 HOW SUPPLIED/STORAGE AND HANDLING

16.1 How Supplied

AMONDYS 45 injection is supplied in single dose vials. The solution is a clear to slightly opalescent, colorless liquid, and may contain trace amounts of small, white to off-white amorphous particles.

• Single-dose vials containing 100 mg/2 mL (50 mg/mL) NDC 60923-227-02

16.2 Storage and Handling

Store AMONDYS 45 at 2°C to 8°C (36°F to 46°F). Do not freeze. Store in original carton until ready for use to protect from light.

17 PATIENT COUNSELING INFORMATION

Hypersensitivity Reactions

Advise patients and/or caregivers that hypersensitivity reactions, including angioedema and anaphylaxis, have occurred in patients who were treated with AMONDYS 45. Instruct them to seek immediate medical care should they experience signs and symptoms of hypersensitivity [see Warnings and Precautions (5.1)].

Kidney Toxicity

Inform patients nephrotoxicity has occurred with drugs similar to AMONDYS 45. Advise patients of the importance of monitoring for kidney toxicity by their healthcare providers during treatment with AMONDYS 45 [see Warnings and Precautions (5.2)].

Manufactured for:
Sarepta Therapeutics, Inc.
Cambridge, MA 02142 USA

Sarepta and Sarepta Therapeutics are trademarks of Sarepta Therapeutics, Inc. registered in the U.S. Patent and Trademark Office and may be registered in various other jurisdictions. AMONDYS 45 and the AMONDYS 45 logo are trademarks of Sarepta Therapeutics, Inc.

Principal Display Panel - 2 mL Carton Label

NDC: 60923-227-02

Rx Only

Amondys 45
(casimersen) Injection

100 mg/2 mL
(50 mg/mL)

For Intravenous Infusion
After Dilution

Use a 0.2 micron in-line
filter during infusion

Single Dose

1 vial

SAREPTA
THERAPEUTICS

Principal Display Panel - 2 mL Vial Label

AMONDYS 45
(casimersen) Injection

100 mg/2 mL
(50 mg/mL)

Rx Only

Single Dose.

Mfg for: Sarepta Therapeutics,
Inc., Cambridge, MA 02142